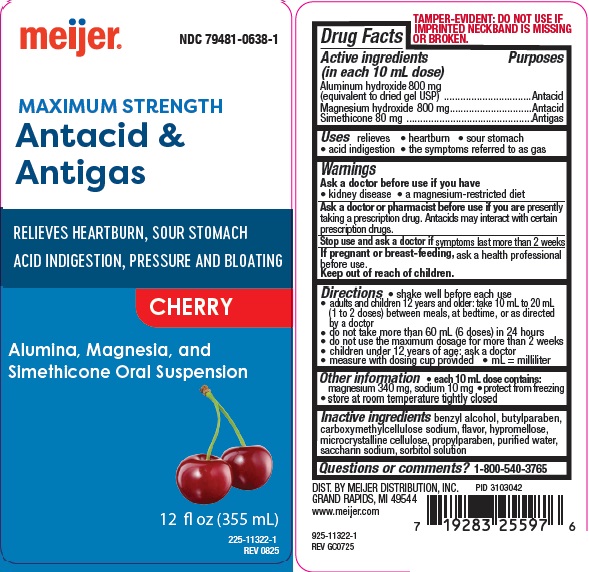 DRUG LABEL: Maximum Strength Antacid and Antigas
NDC: 79481-0638 | Form: SUSPENSION
Manufacturer: Meijer, Inc.
Category: otc | Type: HUMAN OTC DRUG LABEL
Date: 20250730

ACTIVE INGREDIENTS: ALUMINUM HYDROXIDE 800 mg/10 mL; MAGNESIUM HYDROXIDE 800 mg/10 mL; DIMETHICONE 80 mg/10 mL
INACTIVE INGREDIENTS: BENZYL ALCOHOL; BUTYLPARABEN; CARBOXYMETHYLCELLULOSE SODIUM; HYPROMELLOSES; CELLULOSE, MICROCRYSTALLINE; PROPYLPARABEN; WATER; SACCHARIN SODIUM; SORBITOL SOLUTION

mei antacid max cherry

Active ingredients (in each 10 mL teaspoonful)

Aluminum hydroxide (equivalent to dried gel, USP) 800 mg

Magnesium hydroxide 800 mg

Simethicone 80 mg

Purposes

Antacid

Antigas

Uses

relieves

- heartburn
- sour stomach
- acid indigestion
- the symptoms referred to as gas

Warnings

Ask a doctor before use if you have

• kidney disease

• a magnesium-restricted diet

Ask a doctor or pharmacist before use if you are presently taking a prescription drug.

Antacids may interact with certain prescription drugs.

Stop use and ask a doctor if symptoms last more than 2 weeks

If pregnant or breast-feeding, ask a health professional before use.

Keep out of reach of children.

Directions

- shake well before use
- adults and children 12 years and older: take 10 mL to 20 mL (1 to 2 doses) between meals, at bedtime, or as directed by a doctor
- do not take more than 60 mL (6 doses) in 24 hours
- do not use the maximum dosage for more than 2 weeks
- children under 12 years of age: ask a doctor
- measure with dosing cup provided
- mL = milliliter

Other information

- each 10 mL teaspoonful contains: magnesium 340 mg, sodium 10 mg
- protect from freezing
- store at room temperature tightly closed

Inactive ingredients

benzyl alcohol, butylparaben, carboxymethylcellulose sodium, flavor, hypromellose, microcrystalline cellulose, propylparaben, purified water, saccharin sodium, sorbitol solution

Questions or Comments?

1-800-540-3765